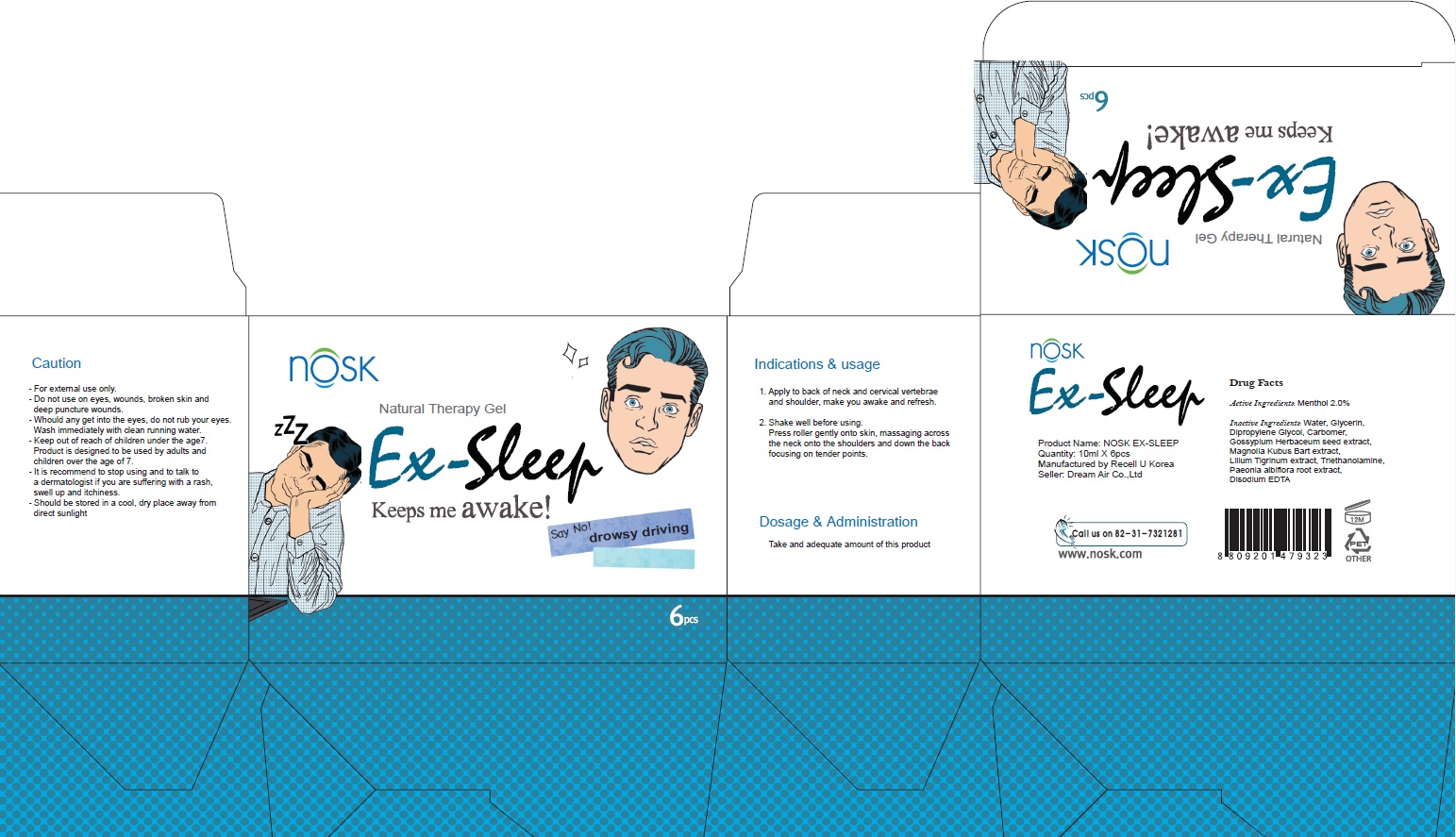 DRUG LABEL: Nosk EX Sleep
NDC: 70767-010 | Form: LIQUID
Manufacturer: DreamAir Co.,
Category: otc | Type: HUMAN OTC DRUG LABEL
Date: 20160614

ACTIVE INGREDIENTS: Menthol 0.2 g/10 mL
INACTIVE INGREDIENTS: Water; Alcohol

ACTIVE INGREDIENT

Active Ingredient: Menthol 2.0%

INACTIVE INGREDIENT

Inactive Ingredients: Water, Alcohol, Glycerin, Dipropylene glycol, Gossypium Herbaceum(cotton) seed extract, Magnolia Kubus Bark extract, Lilium tigrinum extract, Paeonia albiflora root extract, Carbomer, Disodium EDTA, Triethanolamine

PURPOSE

Purpose: Skin Refresher

Caution

Caution: - For the external use only . - Do not apply to eyes ,wounds , broken skin and deep puncture wounds - For 7 years and older only. - When using this product do not get into eyes, Stop use and ask a doctor if rash occurs - Keep out of reach of children - It is recommend to stop applying and to talk to dermatologist immediately if you are suffering such conditions a rash, swell up and itchness - Do not leave it on high, low temperature or exposed on sunlight

KEEP OUT OF REACH OF CHILDREN

INDICATIONS & USAGE

Indications and usage: 1. Apply to back of neckand, cervical vertebrae and shoulder , make you awake and refreshment. 2. Shake well up and down before use Push a little the ball on apply , liquid easily out.

DOSAGE & ADMINISTRATION

Dosage and administration: Take an adequate amount of this product.